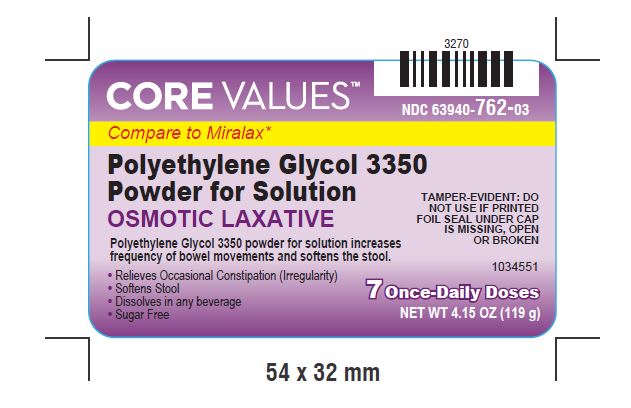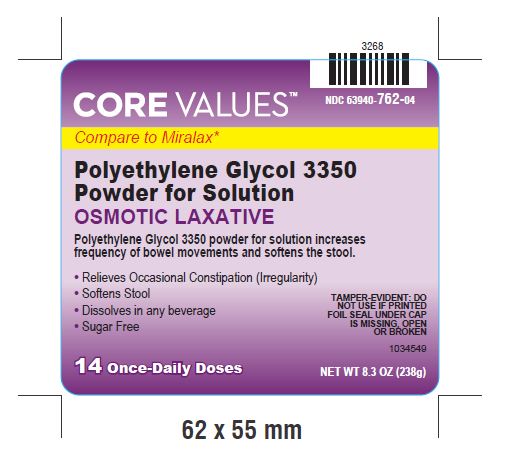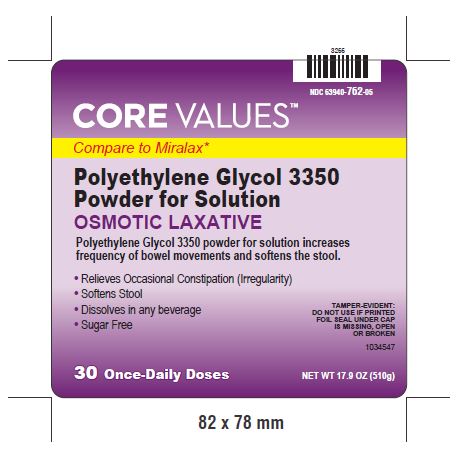 DRUG LABEL: Polyethylene Glycol
NDC: 63940-762 | Form: POWDER, FOR SOLUTION
Manufacturer: Harmon Stores, Inc
Category: otc | Type: HUMAN OTC DRUG LABEL
Date: 20170504

ACTIVE INGREDIENTS: POLYETHYLENE GLYCOL 3350 17 g/17 g

Polyethylene Glycol 3350 powder for solution

Drug Facts

Active ingredient (in each dose)

Polyethylene Glycol 3350, 17 g (cap filled to line)

Purpose

Osmotic Laxative

Use

- relieves occasional constipation (irregularity)
- generally produces a bowel movement in 1 to 3 days

WARNINGS

Allergy alert

Do not use if you are allergic to polyethylene glycol

Do not use if you have kidney disease, except under the advice and supervision of a doctor

Ask a doctor before use if you have

- nausea, vomiting or abdominal pain
- a sudden change in bowel habits that lasts over 2 weeks
- irritable bowel syndrome

Ask a doctor of pharmacist before use if you are taking a prescription drug

- When using this product you may have loose, watery, more frequent stools

Stop use and ask a doctor if

- you have rectal bleeding or your nausea, bloating, cramping or abdominal pain gets worse. These may be signs of a serious condition.
- you get diarrhea
- you need to use a laxative for longer than 1 week

If pregnant or breast-feeding, ask a health professional before use.

Directions

- do not take more than directed unless advised by your doctor
- the bottle top is a measuring cap marked to contain 17 grams of powder when filled to the indicated line (white section in cap)
- adults and children 17 years of age and older:
  - fill to top of white section in cap which is marked to indicate the correct dose (17 g)
  - stir and dissolve in any 4 to 8 ounces of beverage (cold, hot or room temperature) then drink
  - use once a day
  - use no more than 7 days
- children 16 years of age or under: ask a doctor

Other information

- store at 20° to 25°C (68° to 77°F)
- tamper-evident: do not use if foil seal under cap, printed with "SEALED for YOUR PROTECTION" is missing, open or broken

Inactive Ingredient

none

Questions or comments?

1-877-753-3935

Made in India

*Miralax® is a registered trademark of Bayer Consumer Care Holdings LLC

Distributed by Liberty

Procurement, Inc.650 Liberty

Ave. Union, NJ 07083 USA

Visit us at: www.facevalues.com

Revised: 01/2017

PACKAGE LABEL.PRINCIPAL DISPLAY PANEL

NDC 63940-762-03

Polyethylene Glycol 3350

Powder for Solution

OSMOTIC LAXATIVE

Polyethylene Glycol 3350 powder for solution increases frequency of bowel movements and softens the stool.

- Relieves Occasional Constipation (Irregularity)
- Softens Stool
- Dissolves in any beverage
- Sugar Free

TAMPER-EVIDENT: DO NOT USE IF PRINTED FOIL SEAL UNDER CAP IS MISSING, OPEN OR BROKEN

7 Once-Daily Doses

NET WT 4.15 OZ (119 g)

PACKAGE LABEL.PRINCIPAL DISPLAY PANEL

NDC 63940-762-04

Polyethylene Glycol 3350

Powder for Solution

OSMOTIC LAXATIVE

Polyethylene Glycol 3350 powder for solution increases frequency of bowel movements and softens the stool.

- Relieves Occasional Constipation (Irregularity)
- Softens Stool
- Dissolves in any beverage
- Sugar Free

TAMPER-EVIDENT: DO NOT USE IF PRINTED FOIL SEAL UNDER CAP IS MISSING, OPEN OR BROKEN

14 Once-Daily Doses

NET WT 8.3 OZ (238 g)

PACKAGE LABEL.PRINCIPAL DISPLAY PANEL

NDC 63940-762-05

Polyethylene Glycol 3350

Powder for Solution

OSMOTIC LAXATIVE

Polyethylene Glycol 3350 powder for solution increases frequency of bowel movements and softens the stool.

- Relieves Occasional Constipation (Irregularity)
- Softens Stool
- Dissolves in any beverage
- Sugar Free

TAMPER-EVIDENT: DO NOT USE IF PRINTED FOIL SEAL UNDER CAP IS MISSING, OPEN OR BROKEN

30 Once-Daily Doses

NET WT 17.9 OZ (510 g)